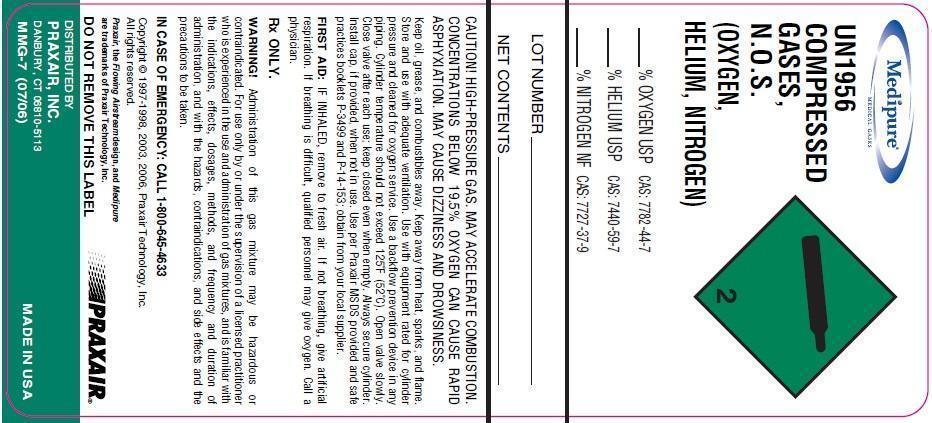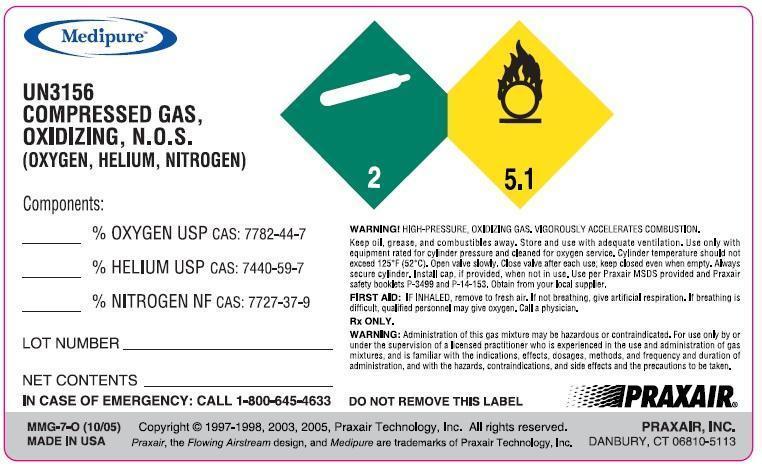 DRUG LABEL: Helium Oxygen Nitrogen mixture
NDC: 49972-010 | Form: GAS
Manufacturer: Praxair Distribution Southeast LLC
Category: prescription | Type: HUMAN PRESCRIPTION DRUG LABEL
Date: 20130729

ACTIVE INGREDIENTS: HELIUM 200 mL/1 L; OXYGEN 500 mL/1 L; NITROGEN 300 mL/1 L

Helium Oxygen Nitrogen Mixture

PACKAGE LABEL

UN1956

GASES,

N.O.S.

(OXYGEN,

HELIUM, NITROGEN)

% OXYGEN USP CAS: 7782-44-7

% HELIUM USP CAS: 7740-59-7

% NITROGEN NF CAS: 7727-37-9

NET CONTENTS

LOT NUMBER

CAUTION! HIGH-PRESSURE GAS. MAY ACCELERATE COMBUSTION. CONCENTRATIONS BELOW 19.5% OXYGEN CAN CAUSE RAPID ASPHYXIATION MAY CAUSE DIZZINESS AND DROWSINESS.

Keep oil, grease, and combustibles away. Keep away from heat, sparks, and flame. Store and use with adequate ventilation. Use with equipment rated for cylinder pressure and cleaned for oxygen service. Use a backflow prevention device in any piping. Cylinder temperature should not exceed 125°F (52°C). Open valve slowly. Close valve after each use; keep closed even when empty. Always secure cylinder. Install cap, if provided, when not in use. Use per Praxair MSDS provided and safe practices booklets P-3499 and P-14-153; obtain from your local supplier.

FIRST AID: IF INHALED, remove to fresh air. If not breathing, give artificial respiration. If breathing is difficult, qualified personnel may give oxygen. Call a physician.

RX ONLY

WARNING! Administration of this gas mixture may be hazardous or contraindicated. For use only by or under the supervision of a licensed

practitioner who is experienced in the use and administration of gas mixtures and is familiar with the indications, effects, dosages, methods and

frequency and duration of administration, and with the hazards, contraindications, and side effects and the precautions to be taken.

Rx only IN CASE OF EMERGENCY CALL 1-800-645-4633

Copyright @ 1997-1998, 2003, 2006, Praxair Technology, Inc.

DO NOT REMOVE THIS LABEL MMG-7 (07/06)

Praxair, the flowing airstream design and Medipure are trademarks of Praxair Technology, Inc. DISTRIBUTED BY PRAXAIR, INC, DANBURY, CT 06810-5113

PACKAGE LABEL

UN3156

COMPRESSED GAS,

OXIDIZING N.O.S.

(OXYGEN, HELIUM, NITROGEN)

% OXYGEN USP CAS: 7782-44-7

% HELIUM USP CAS: 7740-59-7

% NITROGEN NF CAS: 7727-37-9

NET CONTENTS

LOT NUMBER

WARNING! HIGH-PRESSURE OXIDIZING GAS. VIGOROUSLY ACCELERATES COMBUSTION

Keep oil, grease, and combustibles away. Store and use with adequate ventilation. Use only with equipment rated for cylinder pressure and cleaned for oxygen service. Cylinder temperature should not exceed 125°F (52°C). Open valve slowly. Close valve after each use; keep closed even when empty. Always secure cylinder. Install cap, if provided, when not in use. Use per Praxair MSDS provided and safe practices booklets P-3499 and P-14-153; obtain from your local supplier.

FIRST AID: IF INHALED, remove to fresh air. If not breathing, give artificial respiration. If breathing is difficult, qualified personnel may give oxygen. Call a physician.

RX ONLY

WARNING! Administration of this gas mixture may be hazardous or contraindicated. For use only by or under the supervision of a licensed

practitioner who is experienced in the use and administration of gas mixtures and is familiar with the indications, effects, dosages, methods and

frequency and duration of administration, and with the hazards, contraindications, and side effects and the precautions to be taken.

Rx only IN CASE OF EMERGENCY CALL 1-800-645-4633

Copyright @ 1997-1998, 2003, 2005, Praxair Technology, Inc.

DO NOT REMOVE THIS LABEL MMG-7-0 (10/05)

Praxair, the flowing airstream design and Medipure are trademarks of Praxair Technology, Inc. DISTRIBUTED BY PRAXAIR, INC, DANBURY, CT 06810-5113